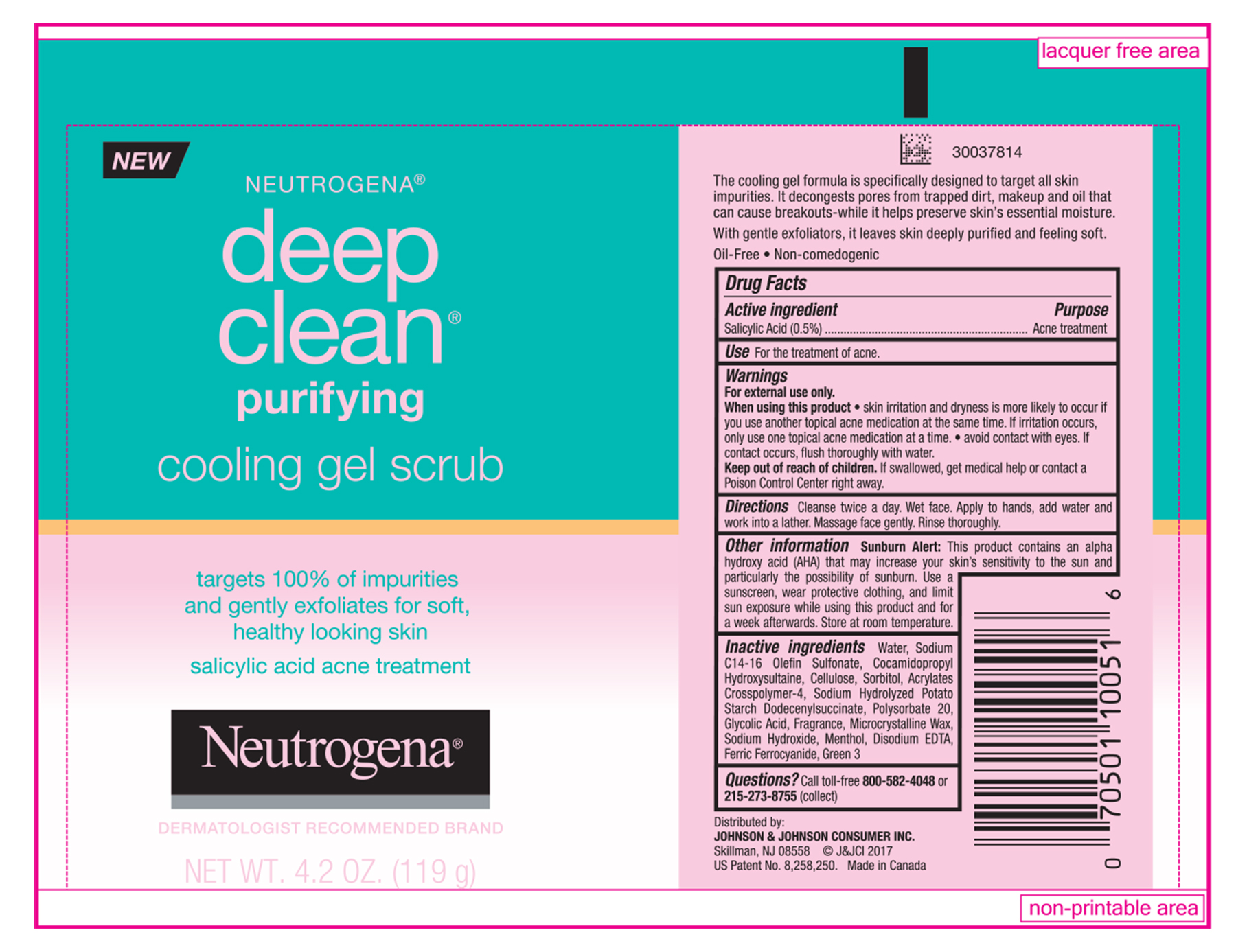 DRUG LABEL: Neutrogena deep clean purifying cooling gel scrub
NDC: 69968-0740 | Form: GEL
Manufacturer: Kenvue Brands LLC
Category: otc | Type: HUMAN OTC DRUG LABEL
Date: 20241112

ACTIVE INGREDIENTS: SALICYLIC ACID 5 mg/1 g
INACTIVE INGREDIENTS: WATER; SODIUM C14-16 OLEFIN SULFONATE; COCAMIDOPROPYL HYDROXYSULTAINE; POWDERED CELLULOSE; SORBITOL; POLYSORBATE 20; GLYCOLIC ACID; MICROCRYSTALLINE WAX; MENTHOL, UNSPECIFIED FORM; SODIUM HYDROXIDE; FERRIC FERROCYANIDE; EDETATE DISODIUM ANHYDROUS; FD&C GREEN NO. 3

Neutrogena® deep clean® purifying cooling gel scrub

Drug Facts

Active ingredient

Salicylic Acid 0.5%

Purpose

Acne treatment

Use

For the treatment of acne.

Warnings

For external use only.

When using this product

- skin irritation and dryness is more likely to occur if you use another topical acne medication at the same time. If irritation occurs, only use one topical acne medication at a time.
- avoid contact with eyes. If contact occurs, flush thoroughly with water.

Keep out of reach of children. If swallowed, get medical help or contact a Poison Control Center right away.

Directions

Cleanse twice a day. Wet face. Apply to hands, add water and work into a lather. Massage face gently. Rinse thoroughly

Other information

Sunburn Alert

This product contains an alpha hydroxy acid (AHA) that may increase your skin's sensitivity to the sun and particularly the possibility of sunburn. Use a sunscreen, wear protective clothing, and limit sun exposure while using this product and for a week afterwards. Store at room temperature.

Inactive ingredients

Water, Sodium C14-16 Olefin Sulfonate, Cocamidopropyl Hydroxysultaine, Cellulose Sorbitol, Acrylates Crosspolymer-4, Sodium Hydrolyzed Potato Starch Dodecenylsuccinate, Polysorbate 20, Glycolic Acid, Fragrance, Microcrystalline Wax, Sodium Hydroxide, Menthol, Disodium EDTA, Ferric Ferrocyanide, Green 3

Questions?

Call toll-free 800-582-4048 or 215-273-8755 (collect)

Distributed by:
JOHNSON & JOHNSON CONSUMER INC.
Skillman, NJ 08558

PRINCIPAL DISPLAY PANEL - 119 g Tube Label

NEW
NEUTROGENA®
deep
clean®
purifying
cooling gel scrub
targets 100% of impurities
and gently exfoliates for soft,
healthy looking skin

salicylic acid acne treatment

Neutrogena®
DERMATOLOGIST RECOMMENDED BRAND
NET WT. 4.2 OZ. (119 g)